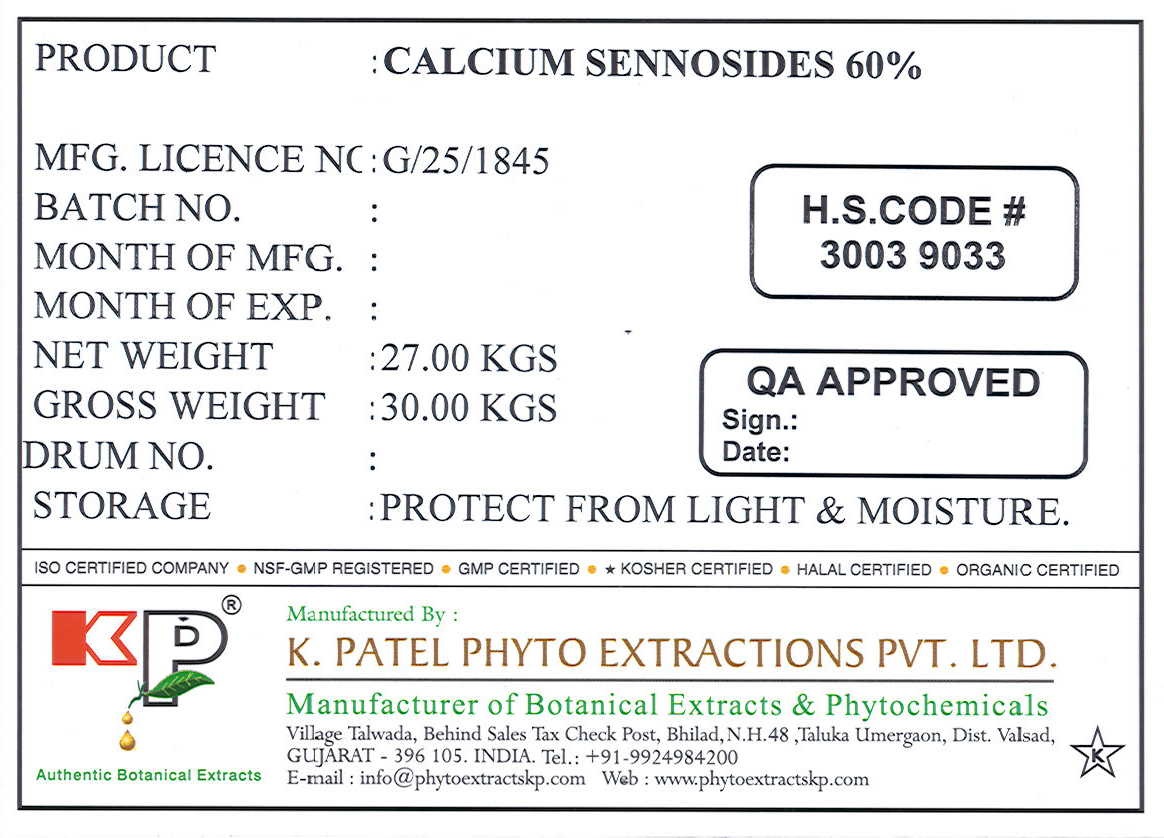 DRUG LABEL: Calcium Sennosides
NDC: 73276-002 | Form: POWDER
Manufacturer: K. Patel Phyto Extractions Private Limited
Category: other | Type: BULK INGREDIENT
Date: 20230110

ACTIVE INGREDIENTS: SENNOSIDES 27 kg/27 kg

Calcium Sennosides 60 %